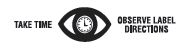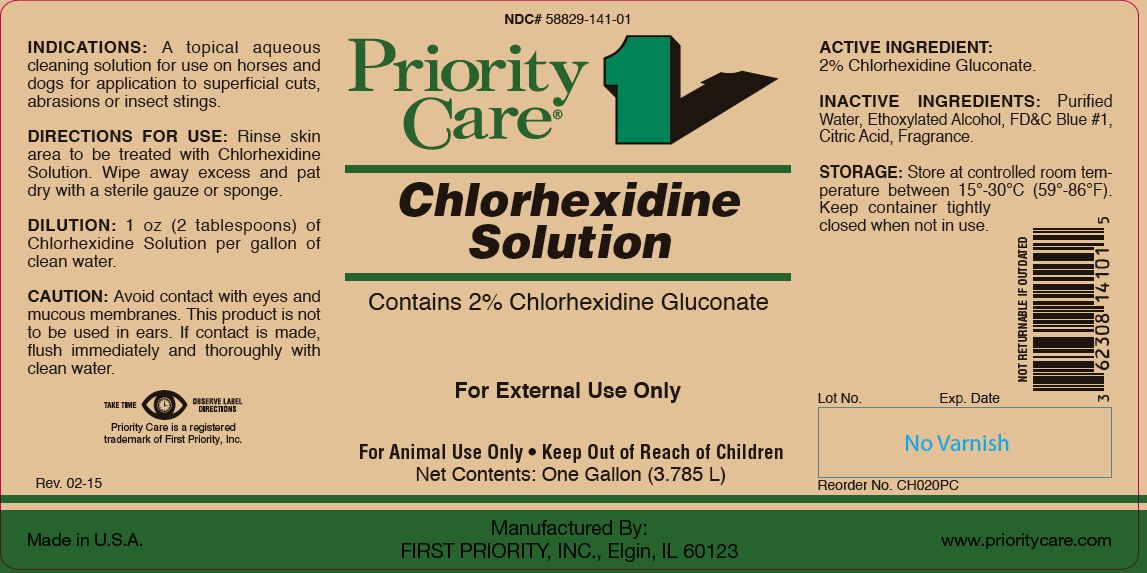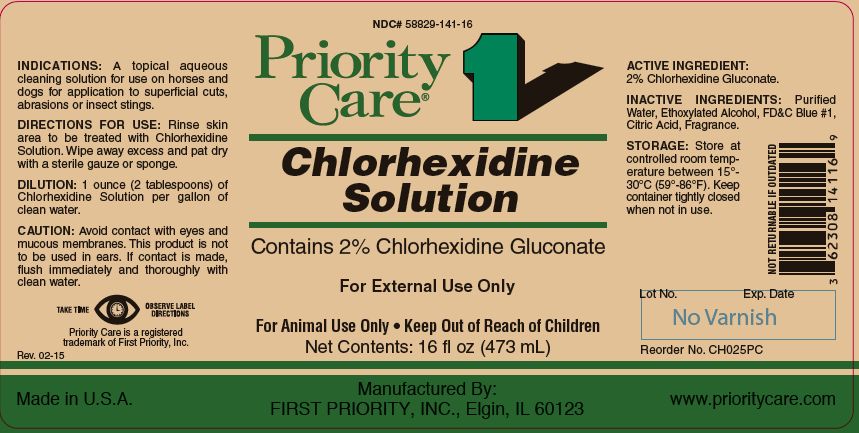 DRUG LABEL: CHLORHEXIDINE
NDC: 58829-141 | Form: SOLUTION
Manufacturer: FIRST PRIORITY INCORPORATED
Category: animal | Type: OTC ANIMAL DRUG LABEL
Date: 20191014

ACTIVE INGREDIENTS: CHLORHEXIDINE GLUCONATE 99.0 g/1 L

Chlorhexidine Solution

INFORMATION FOR OWNERS/CAREGIVERS

Contains 2% Chlorhexidine Gluconate

KEEP OUT OF REACH OF CHILDREN

For External Use Only

For Animal Use Only • Keep Out of Reach of Children

INDICATIONS:

A topical aqueous cleaning solution for use on horses and dogs for application to superficial cuts, abrasions or insect stings.

DIRECTIONS FOR USE:

Rinse skin area to be treated with Chlorhexidine Solution. Wipe away excess and pat dry with a sterile gauze or sponge.

DILUTION:

1 oz (2 tablespoons) of Chlorhexidine Solution per gallon of clean water.

CAUTION:

Avoid contact with eyes and mucous membranes. This product is not to be used in ears. If contact is made, flush immediately and thoroughly with clean water.

ACTIVE INGREDIENT:

2% Chlorhexidine Gluconate.

INACTIVE INGREDIENTS:

Purified Water, Ethoxylated Alcohol, FD&C Blue #1, Citric Acid, Fragrance.

STORAGE:

Store at controlled room temperature between 15º to 30ºC (59º-86ºF). Keep container tightly closed when not in use.

Net Contents:

16 fl oz (473 mL) Reorder No. CH025PC

One Gallon (3.785 L) Reorder No. CH020PC

INFORMATION FOR OWNERS/CAREGIVERS

Priority Care is a registered trademark of First Priority, Inc.

Made in U.S.A.

Manufactured By: FIRST PRIORITY, INC., Elgin, IL 60123

www.prioritycare.com